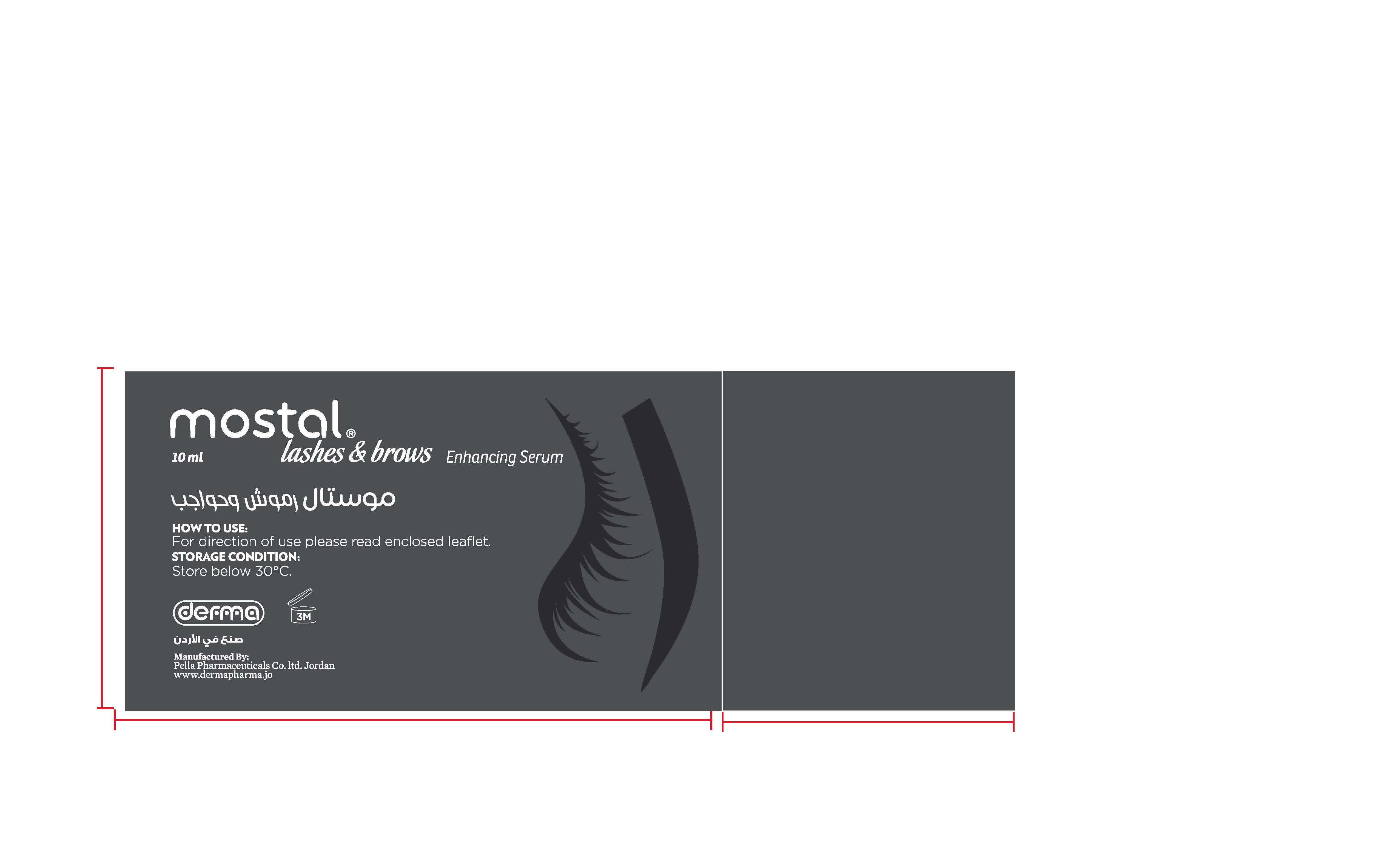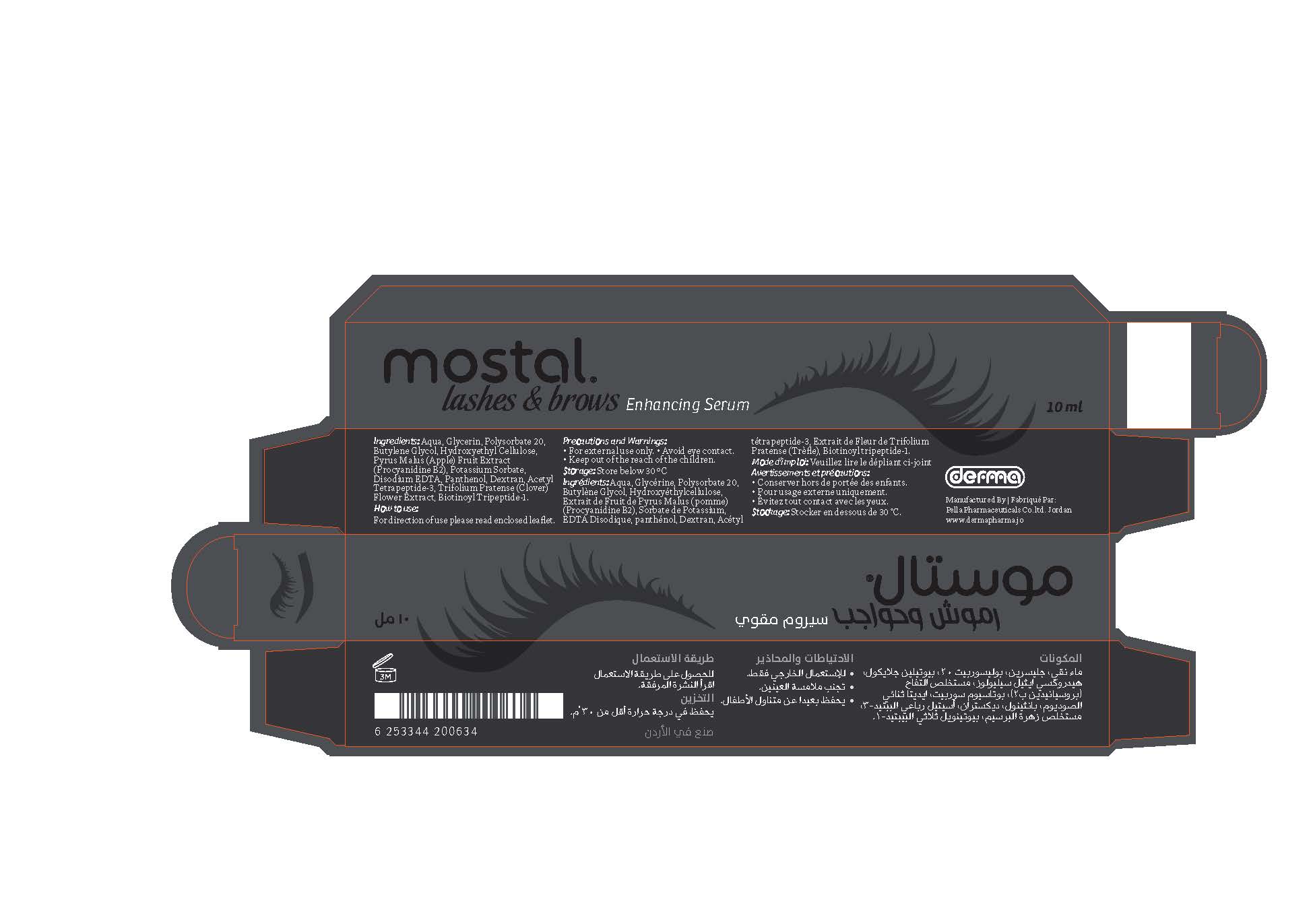 DRUG LABEL: Mostal Lashes and Brows Enhancing Serum
NDC: 82160-634 | Form: GEL
Manufacturer: Pella Pharmaceuticals Co. Ltd
Category: otc | Type: HUMAN OTC DRUG LABEL
Date: 20241231

ACTIVE INGREDIENTS: ACETYL TETRAPEPTIDE-3 1 mg/10 mL; BIOTINOYL TRIPEPTIDE-1 0.066 mg/10 mL; APPLE 100 mg/10 mL
INACTIVE INGREDIENTS: WATER; EDETATE DISODIUM ANHYDROUS; DEXPANTHENOL; TRIFOLIUM PRATENSE FLOWER; BUTYLENE GLYCOL; HYDROXYETHYL CELLULOSE, UNSPECIFIED; DEXTRAN 40; GLYCERIN; POLYSORBATE 20; POTASSIUM SORBATE

Mostal Lashes

Forms and Presentation

Plastic serum tube with brush 10 ml

Purpose

Lashes and brows enhancing serum

Active Ingredients

Pyrus Malus (Apple) Fruit Extract (Procyanidine B2)

Acetyl Tetrapiptide-3

Biotinoyl Tripeptide-1

Composition

Aqua, Glycerin, Polysorbate 20, Butylene Glycol, Hydroxyethyl Cellulose, Potassium Sorbate, Disodium EDTA, Panthenol, Dextran, Trifolium Pratense (Clover) Flower Extract.

Properties

Advanced revitalizing formula for longer, stronger, fuller lashes and brows, formulated with a powerful peptide complex and vitamins with natural vegan extracts work together for longer, fuller and more voluminous lashes and bolder brows.
Does not change eyelash or brow color, Paraben Free

Indication

Mostal lashes & brows serum is revolutionary serum of lashes and brows enhancing, conditioning, moisturizing and strengthening ingredients that work together to help improve the overall appearance of the eyelashes and eyebrows.
Five key ingredients benefits:

- Pyrus Malus (Apple) Fruit Extract (Procyanidine B2): Helps to stop hair loss from eyelashes and eyebrows, improves their growth and increase their density.
- Panthenol: Moisturizes and strengthens hair; improves texture, suppleness and sheen; increases durability and flexibility.
- Acetyl Tetrapeptide-3: Helps to promote regrowth and build stronger cellular matrices around the dermal papilla, which means that lashes and brows will be better anchored for less chance of fall out.
- Biotionyl Tripeptide-1: Helps lashes and brows appear longer, fuller and stronger. Promotes hair bulb keratinocyte production and ensures optimal hair anchorage, helping lashes reach their full potential.
- Trifolium Pratense (Clover) Flower Extract: thanks to its high content of Biochanin A isoflavone, has showed antioxidant properties useful in fighting free radicals, counteracting the damage created by the external environment and stressful conditions.

Contraindication

Hypersensitivity to any of the components

Precautions

- Must only be used as directed.
- Do not use if the packaging has been damaged.

Precaution

Keep out of reach of children

Side effects

There are no known side effects.

Dosage and administration

For best results apply it once in the morning and once in the evening. The eye and brows should completely clean of any makeup.

For eyelashes: Apply a thin line along the outer base of the upper and lower lash line using the applicator brush and allow 1 – 2 minutes for serum to dry.

For eyebrows: Apply serum using the applicator along your natural brow line, use enough to dampen eyebrows and gently massage with fingertips and allow 1 – 2 minutes for serum to dry.

To achieve thicker, fuller and longer eyelashes and eyebrows in just 4 – 6 weeks with full improvement in 3 months.

Storage Condition

Store below 30◦C.

Warnings

- For external use only.
- Avoid contact with eyes. Rinse thoroughly with water in the event of contact with the eyes.
- Discontinue use if irritation (redness, pain, etc.) occurs. If skin irritation occurs, consult your physician if the symptoms persist for more than 48 hr.